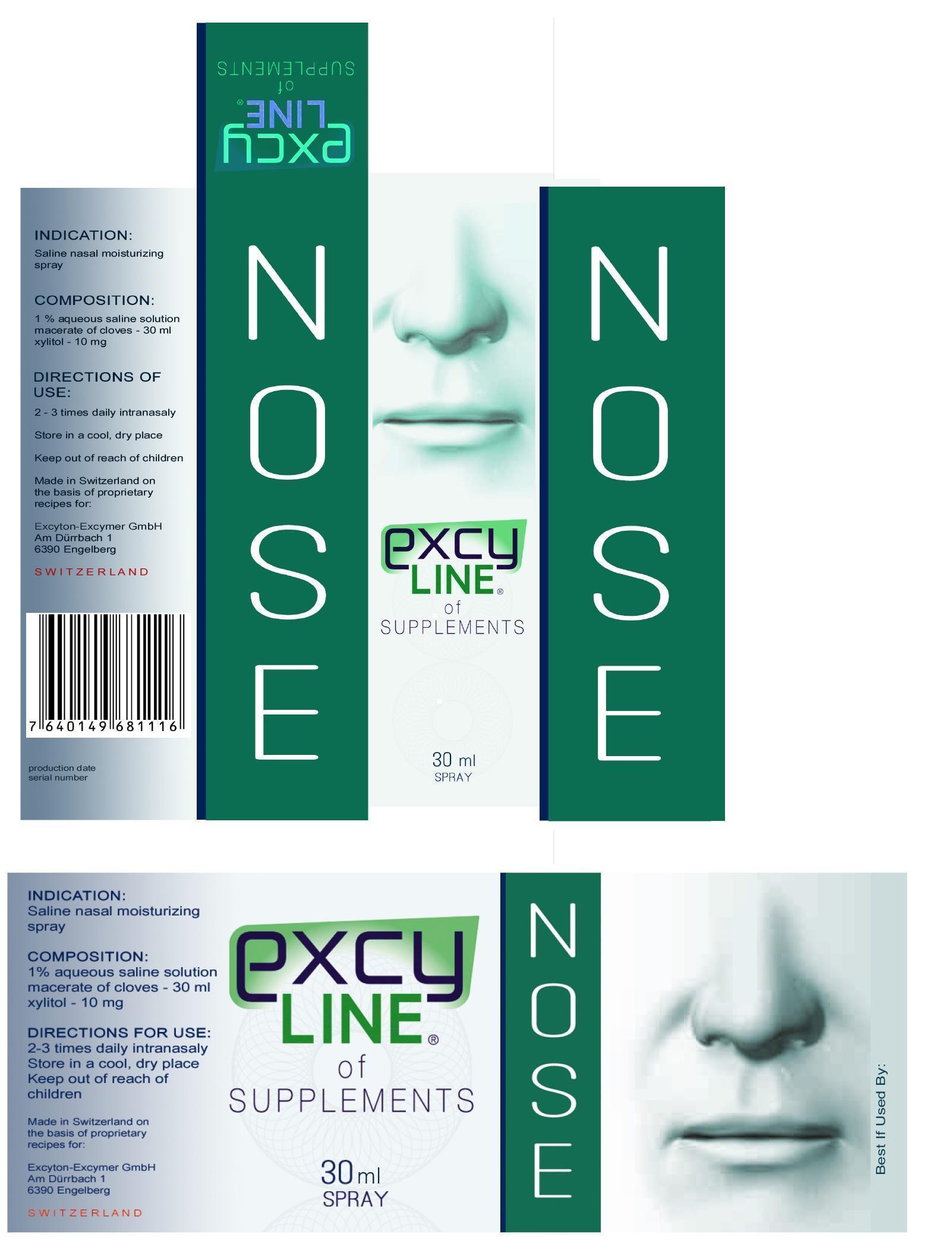 DRUG LABEL: Nose
NDC: 59430-101 | Form: AEROSOL
Manufacturer: US EXCY-LINE INC.
Category: otc | Type: HUMAN OTC DRUG LABEL
Date: 20130927

ACTIVE INGREDIENTS: CLOVE .75 mg/100 mL
INACTIVE INGREDIENTS: Xylitol

Drug Fact

ACTIVE INGREDIENT

Clove

PURPOSE

Nasal Moisturizer

KEEP OUT OF REACH OF CHILDREN

INDICATIONS & USAGE

Nasal moisturizer & Intranasaly

WARNINGS

do not use more than directed

DOSAGE & ADMINISTRATION

2-3 times daily intranasaly

Inactive Ingredient

Xylitol